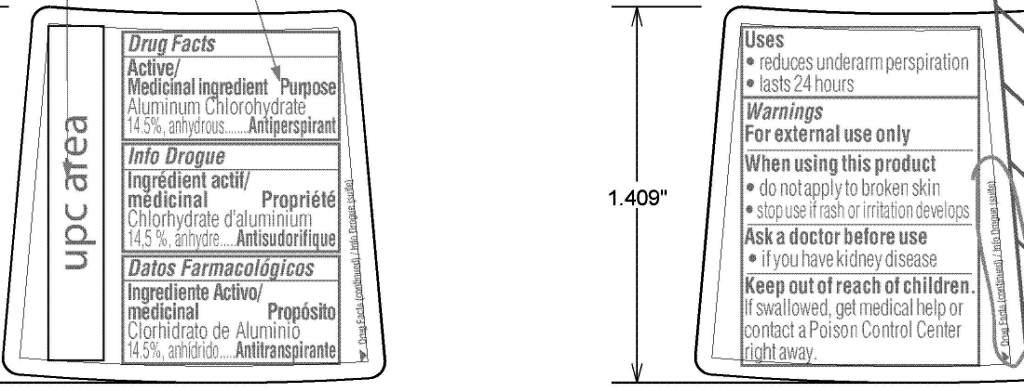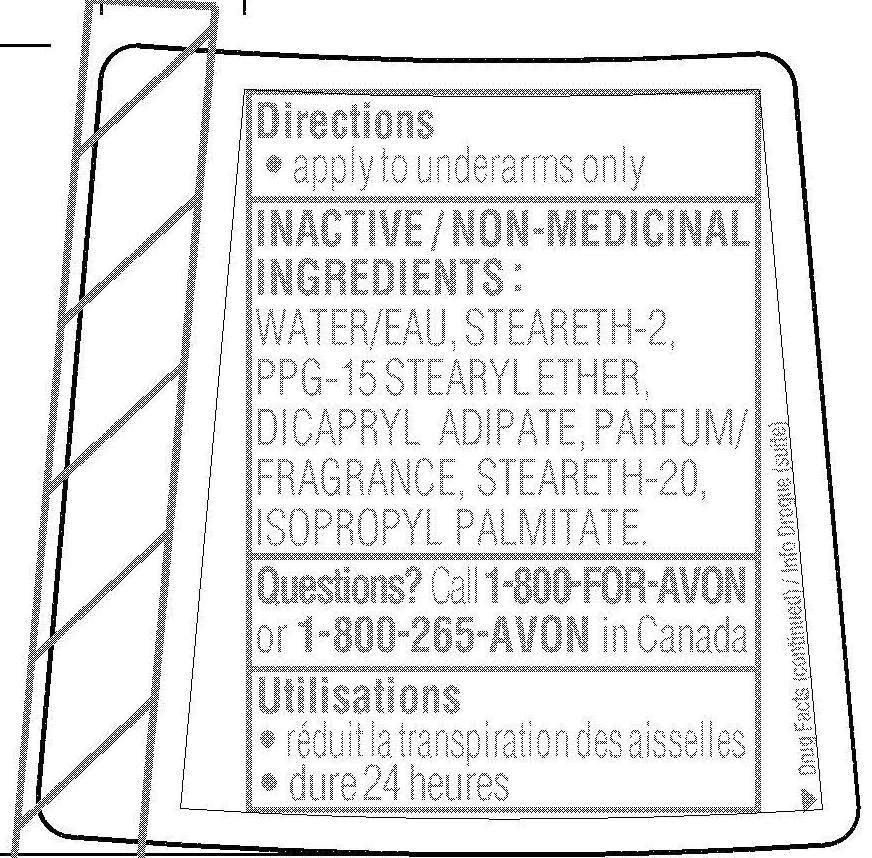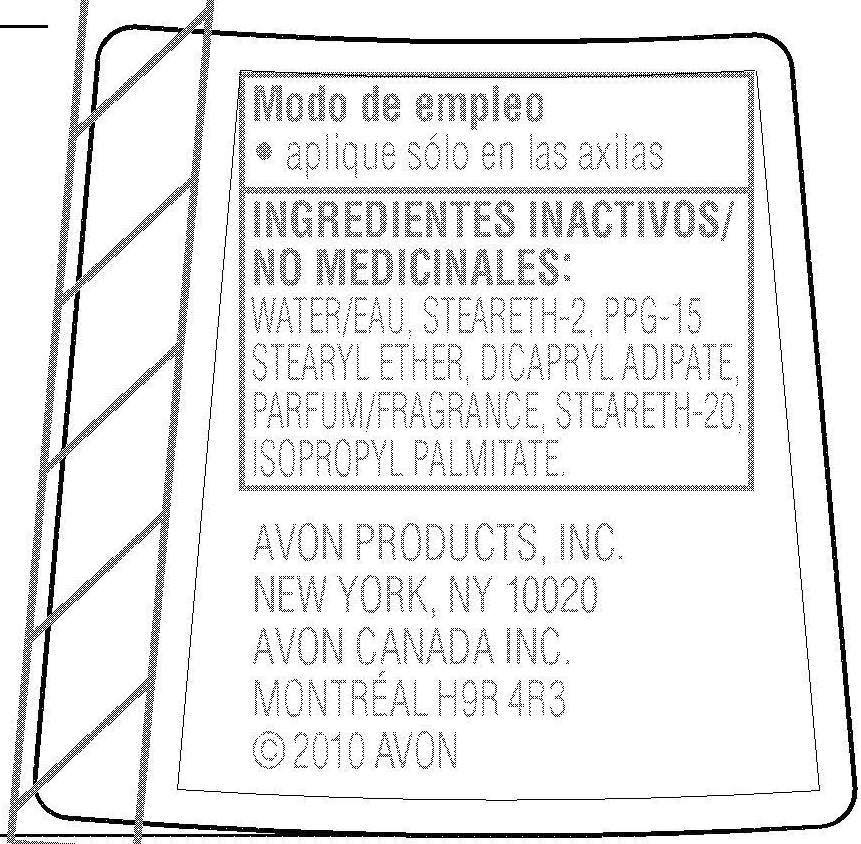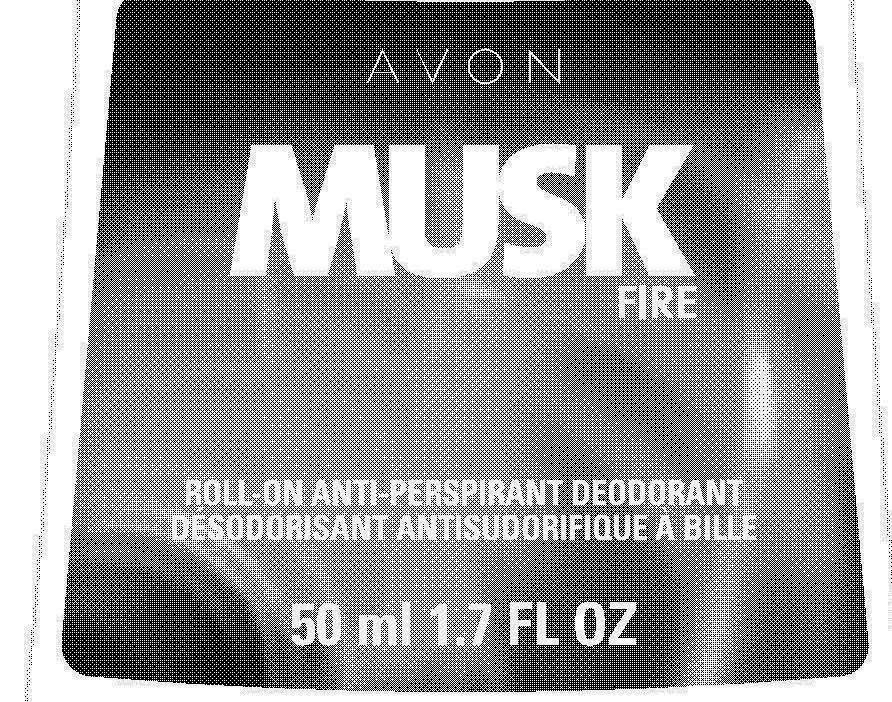 DRUG LABEL: Musk Fire
NDC: 10096-0259 | Form: GEL
Manufacturer: Avon Products, Inc.
Category: otc | Type: HUMAN OTC DRUG LABEL
Date: 20110419

ACTIVE INGREDIENTS: ALUMINUM CHLOROHYDRATE 7.25 mL/50 mL

Drug Facts

Active ingredient
Aluminum Chlorohydrate
14.5%, anhydrous...........

Purpose
.............Antiperspirant

Uses
• reduces underarm perspiration
• lasts 24 hours

Warnings
For external use only

When using this product
• do not apply to broken skin
• stop use if rash or irritation develops

Ask a doctor before use
• if you have kidney disease

Keep out of reach of children.
If swallowed, get medical help or
contact a Poison Control Center
right away.

Directions
• apply to underarms only

INACTIVE INGREDIENTS :
WATER/EAU, STEARETH-2,
PPG-15 STEARYL ETHER,
DICAPRYL ADIPATE, PARFUM/
FRAGRANCE, STEARETH-20,
ISOPROPYL PALMITATE.

Questions? Call 1-800-FOR-AVON
or 1-800-265-AVON in Canada